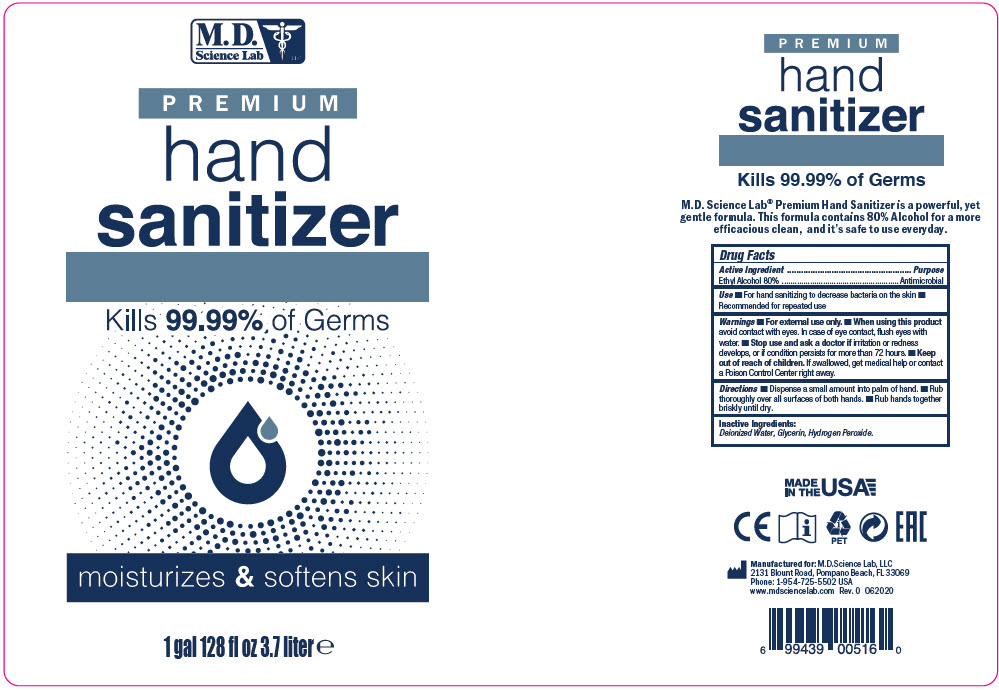 DRUG LABEL: PREMIUM HAND SANITIZER
NDC: 69898-801 | Form: LIQUID
Manufacturer: MD Science Lab LLC
Category: otc | Type: HUMAN OTC DRUG LABEL
Date: 20200629

ACTIVE INGREDIENTS: Alcohol 80 mL/100 mL
INACTIVE INGREDIENTS: Water; Glycerin; POLYETHYLENE GLYCOL 300; ALOE VERA LEAF; .ALPHA.-TOCOPHEROL ACETATE, DL-; TEA TREE OIL

PREMIUM HAND SANITIZER

Drug Facts

Active Ingredient

Ethyl Alcohol 80%

Purpose

Antimicrobial

Use

- For hand sanitizing to decrease bacteria on the skin
- Recommended for repeated use

Warnings

- For external use only.

- When using this product avoid contact with eyes. In case of eye contact, flush eyes with water.

- Stop use and ask a doctor if irritation or redness develops, or if condition persists for more than 72 hours.

- Keep out of reach of children. If swallowed, get medical help or contact a Poison Control Center right away.

Directions

- Dispense a small amount into palm of hand.
- Rub thoroughly over all surfaces of both hands.
- Rub hands together briskly until dry.

Inactive Ingredients

Deionized Water, Glycerin, Hydrogen Peroxide.

PRINCIPAL DISPLAY PANEL - 3.7 liter Bottle Label

M.D.
Science Lab
LLC

PREMIUM
hand
sanitizer

Kills 99.99% of Germs

moisturizes & softens skin

1 gal 128 fl oz 3.7 liter e